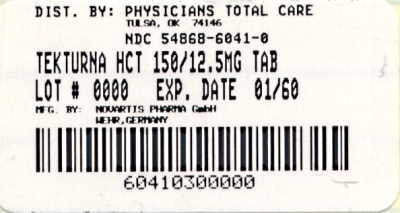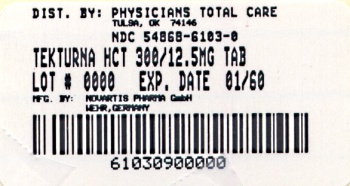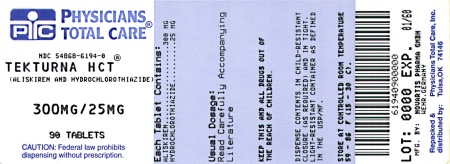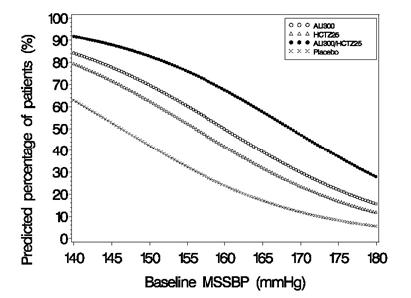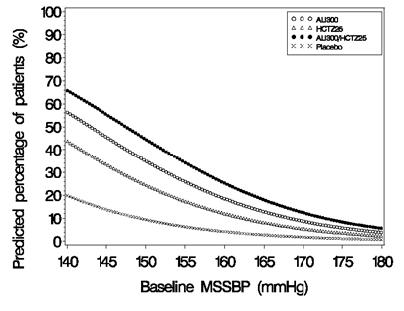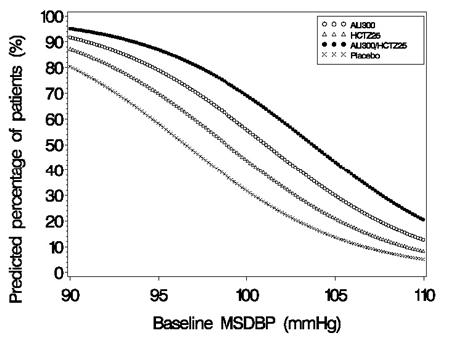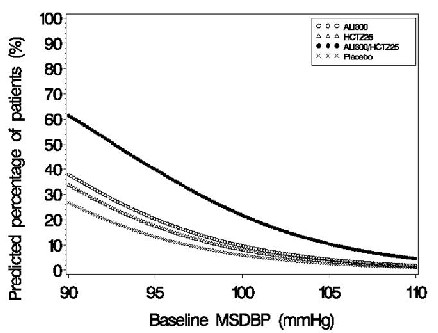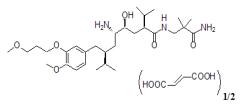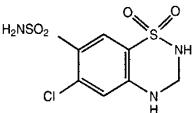 DRUG LABEL: Tekturna HCT
NDC: 54868-6041 | Form: TABLET, FILM COATED
Manufacturer: Physicians Total Care, Inc.
Category: prescription | Type: HUMAN PRESCRIPTION DRUG LABEL
Date: 20090925

ACTIVE INGREDIENTS: ALISKIREN HEMIFUMARATE 150 mg/1 1; HYDROCHLOROTHIAZIDE 12.5 mg/1 1
INACTIVE INGREDIENTS: SILICON DIOXIDE; CROSPOVIDONE; HYPROMELLOSE 2208 (15000 MPA.S); FERRIC OXIDE RED; FERRIC OXIDE YELLOW; FERROSOFERRIC OXIDE; LACTOSE; MAGNESIUM STEARATE; CELLULOSE, MICROCRYSTALLINE; POLYETHYLENE GLYCOL; POVIDONE; TALC; TITANIUM DIOXIDE; STARCH, WHEAT

HIGHLIGHTS OF PRESCRIBING INFORMATION

These highlights do not include all the information needed to use Tekturna HCT safely and effectively. See full prescribing information for Tekturna HCT.
Tekturna HCT (aliskiren and hydrochlorothiazide) Tablets
Initial U.S. Approval: 2008

RECENT MAJOR CHANGES

Indications and Usage (1) 07/2009

Dosage and Administration

Add-On Therapy (2.3) 07/2009

Replacement Therapy (2.4) 07/2009

Initial Therapy (2.5) 07/2009

WARNING: AVOID USE IN PREGNANCY

When pregnancy is detected, discontinue Tekturna HCT as soon as possible. Drugs that act directly on the renin-angiotensin system can cause injury and death to the developing fetus. (5.1)

1 INDICATIONS AND USAGE

Tekturna HCT is a combination of aliskiren, a direct renin inhibitor, and hydrochlorothiazide (HCTZ), a thiazide diuretic, indicated for the treatment of hypertension:

- In patients not adequately controlled with monotherapy
- As initial therapy in patients likely to need multiple drugs to achieve their blood pressure goals (1)

2 DOSAGE AND ADMINISTRATION

- The antihypertensive effect is largely manifested within 1 week, with maximal effects seen at around 4 weeks. If blood pressure remains uncontrolled after 2 to 4 weeks of therapy, titrate up to a maximum of 300/25 mg. (2.2)
- Order of increasing mean effect: 150/12.5 mg, 150/25 mg or 300/12.5 mg, and 300/25 mg (2.1)
- One tablet daily, with a routine pattern with regard to meals. (2.7)
- May be administered with other antihypertensive agents. (2.6)
- Add-on or Initial therapy: Initiate with 150/12.5mg. Titrate as needed up to a maximum of 300/25 mg. (2.3, 2.5)
- Replacement therapy: May be substituted for titrated components (2.4)

3 DOSAGE FORMS AND STRENGTHS

Tablets (mg aliskiren/mg HCTZ): 150/12.5, 150/25, 300/12.5, 300/25 (3)

4 CONTRAINDICATIONS

Anuria (4)

Hypersensitivity to sulfonamide-derived drugs (4)

5 WARNINGS AND PRECAUTIONS

- Head and Neck Angioedema: Discontinue Tekturna HCT and monitor until signs and symptoms resolve. (5.2)
- Hypotension in Volume- or Salt-Depleted Patients: Correct imbalances before initiating therapy with Tekturna HCT. (5.3)
- Patients with Severe Renal Impairment: Not recommended if GFR <30 mL/min. (5.4)
- Patients with Hepatic Impairment: Titrate slowly. (5.5)
- Hypersensitivity Reactions: May occur from HCTZ component (5.6)

6 ADVERSE REACTIONS

The most common adverse reactions (incidence ≥1.5% and more common than with placebo) are: dizziness and diarrhea. (6.1)

To report SUSPECTED ADVERSE REACTIONS, contact Novartis Pharmaceuticals Corporation at 1-888-669-6682 or FDA at 1-800-FDA-1088 or www.fda.gov/medwatch.

7 DRUG INTERACTIONS

Aliskiren:

- Cyclosporine: Concomitant use is not recommended.

Hydrochlorothiazide:

- Alcohol, Barbiturates, Narcotics: Potentiation of orthostatic hypotension
- Antidiabetic Drugs: Dosage adjustment of antidiabetic may be required
- Cholestyramine and Colestipol: Reduced absorption of thiazides
- Corticosteroids, ACTH: Hypokalemia, electrolyte depletion
- Lithium: Reduced renal clearance and high risk of lithium toxicity when used with diuretics. Should not be given with diuretics.
- NSAIDs: Can reduce diuretic, natriuretic, and antihypertensive effects of diuretics. Observe patient closely.

8 USE IN SPECIFIC POPULATIONS

Nursing Mothers: Nursing or drug should be discontinued. (8.3)

FULL PRESCRIBING INFORMATION

WARNING: AVOID USE IN PREGNANCY

When pregnancy is detected, discontinue Tekturna HCT as soon as possible. Drugs that act directly on the renin-angiotensin system can cause injury and death to the developing fetus. [See Warnings and Precautions (5.1)]

1 INDICATIONS AND USAGE

Tekturna HCT is indicated for the treatment of hypertension.

Add-On Therapy

A patient whose blood pressure is not adequately controlled with aliskiren alone or hydrochlorothiazide alone may be switched to combination therapy with Tekturna HCT.

A patient whose blood pressure is controlled with hydrochlorothiazide alone but who experiences hypokalemia may be switched to combination therapy with Tekturna HCT.

A patient who experiences dose-limiting adverse reactions on either component alone may be switched to Tekturna HCT containing a lower dose of that component in combination with the other to achieve similar blood pressure reductions.

Replacement Therapy

Tekturna HCT may be substituted for the titrated components.

Initial Therapy

Tekturna HCT may be used as initial therapy in patients who are likely to need multiple drugs to achieve their blood pressure goals.

The choice of Tekturna HCT as initial therapy should be based on an assessment of potential benefits and risks.

Patients with Stage 2 hypertension are at a relatively high risk for cardiovascular events (such as strokes, heart attacks, and heart failure), kidney failure, and vision problems, so prompt treatment is clinically relevant. The decision to use a combination as initial therapy should be individualized and should be shaped by considerations such as baseline blood pressure, the target goal, and the incremental likelihood of achieving goal with a combination compared to monotherapy. Individual blood pressure goals may vary based upon the patient’s risk.

Data from the high-dose multifactorial study [see Clinical Studies (14)] provides estimates of the probability of reaching a target blood pressure with Tekturna HCT compared to aliskiren or hydrochlorothiazide monotherapy. The figures below provide estimates of the likelihood of achieving systolic or diastolic blood pressure control with Tekturna HCT 300/25 mg, based upon baseline systolic or diastolic blood pressure. The curve of each treatment group was estimated by logistic regression modeling. The estimated likelihood at the right tail of each curve is less reliable because of small numbers of subjects with high baseline blood pressures.

Figure 1: Probability of Achieving Systolic Blood Pressure (SBP) <140 mmHg
Figure 2: Probability of Achieving Systolic Blood Pressure (SBP) <130 mmHg
Figure 3: Probability of Achieving Diastolic Blood Pressure (DBP) <90 mmHg
Figure 4: Probability of Achieving Diastolic Blood Pressure (DBP) <80 mmHg

At all levels of baseline blood pressure, the probability of achieving any given diastolic or systolic goal is greater with the combination than for either monotherapy. For example, the mean baseline msSBP/msDBP for patients participating in this multifactorial study was 154/99 mmHg. A patient with a baseline blood pressure of 154/99 mmHg has about a 62% chance of achieving a goal of <140 mmHg (systolic) and 61% chance of achieving <90 mmHg (diastolic) on aliskiren alone, and the chance of achieving these goals on hydrochlorothiazide alone is about 54% (systolic) and 49% (diastolic). The chance of achieving these goals on Tekturna HCT rises to about 77% (systolic) and 74% (diastolic). The chance of achieving these goals on placebo is about 34% (systolic) and 37% (diastolic). [See Dosage and Administration (2) and Clinical Studies (14).]

2 DOSAGE AND ADMINISTRATION

2.1 Dose Selection

The recommended once-daily doses of Tekturna HCT in order of increasing mean effect are 150/12.5 mg, 150/25 mg or 300/12.5 mg, and 300/25 mg.

2.2 Dose Titration

The antihypertensive effect of Tekturna HCT is largely manifested within 1 week, with maximal effects generally seen at around 4 weeks. If blood pressure remains uncontrolled after 2 to 4 weeks of therapy, the dose may be titrated up to a maximum of aliskiren 300 mg/hydrochlorothiazide 25 mg.

2.3 Add-On Therapy

A patient whose blood pressure is not adequately controlled with aliskiren alone or hydrochlorothiazide alone may be switched to combination therapy with Tekturna HCT. The usual recommended starting dose is 150/12.5 mg once daily as needed to control blood pressure. The dose may be titrated up to a maximum of aliskiren 300 mg/hydrochlorothiazide 25 mg once daily.

2.4 Replacement Therapy

Tekturna HCT may be substituted for the individually titrated components.

2.5 Initial Therapy

The usual recommended starting dose is 150/12.5 mg once daily as needed to control blood pressure. The dose may be titrated up to a maximum of aliskiren 300 mg/hydrochlorothiazide 25 mg once daily.

Tekturna HCT is not recommended for use as initial therapy in patients with intravascular volume depletion. [See Warnings and Precautions (5.3)]

2.6 Use with Other Antihypertensive Drugs

Tekturna HCT may be administered with other antihypertensive agents. There are no data available with use of Tekturna HCT with angiotensin-converting enzyme inhibitors or beta blockers [see Clinical Studies (14)].

2.7 Relationship to Meals

Patients should establish a routine pattern for taking Tekturna HCT with regard to meals. High-fat meals decrease absorption substantially [see Clinical Pharmacology (12.3)].

2.8 Dosing in Specific Populations

Renal Impairment

The usual regimens of Tekturna HCT may be followed as long as the patient’s creatinine clearance is >30 mL/min. In patients with more severe renal impairment, loop diuretics are preferred to thiazides, so Tekturna HCT is not recommended.

Hepatic Impairment

Adjustment of the starting dose is not necessary with hepatic impairment.

Elderly Patients

Adjustment of the starting dose is not required for elderly patients.

3 DOSAGE FORMS AND STRENGTHS

- 150 mg/12.5 mg tablets: white, biconvex ovaloid, film-coated tablets imprinted with NVR/LCI
- 150 mg/25 mg tablets: pale yellow, biconvex ovaloid, film-coated tablets imprinted with NVR/CLL
- 300 mg/12.5 mg tablets: violet white, biconvex ovaloid, film-coated tablets imprinted with NVR/CVI
- 300 mg/25 mg tablets: light yellow, biconvex ovaloid, film-coated tablets imprinted with NVR/CVV

4 CONTRAINDICATIONS

Because of the hydrochlorothiazide component, Tekturna HCT is contraindicated in patients with anuria or hypersensitivity to sulfonamide-derived drugs [see Warnings and Precautions (5.6) and Adverse Reactions (6.1)]. Hypersensitivity reactions may range from urticaria to anaphylaxis [see Adverse Reactions (6.1)].

5 WARNINGS AND PRECAUTIONS

5.1 Fetal/Neonatal Morbidity and Mortality

Tekturna HCT can cause fetal harm when administered to a pregnant woman. If this drug is used during pregnancy, or if the patient becomes pregnant while taking this drug, the patient should be apprised of the potential hazard to the fetus.

Drugs that act directly on the renin-angiotensin system can cause fetal and neonatal morbidity and death when administered to pregnant women. If this drug is used during pregnancy, or if the patient becomes pregnant while taking this drug, apprise the patient of the potential hazard to the fetus. [see Use in Specific Populations (8.1)] In several dozen published cases, ACE inhibitors use during the second and third trimesters of pregnancy was associated with fetal and neonatal injury, including hypotension, neonatal skull hypoplasia, anuria, reversible or irreversible renal failure, and death. In addition, first trimester use of ACE inhibitors has been associated with birth defects. Thiazides cross the placenta, and use of thiazides during pregnancy is associated with a risk of fetal or neonatal jaundice, thrombocytopenia, and possible other adverse reactions that have occurred in adults.

5.2 Head and Neck Angioedema

Aliskiren

Angioedema of the face, extremities, lips, tongue, glottis and/or larynx has been reported in patients treated with Tekturna and has necessitated hospitalization and intubation. This may occur at any time during treatment and has occurred in patients with and without a history of angioedema with ACE inhibitors or angiotensin receptor antagonists. If angioedema involves the throat, tongue, glottis or larynx, or if the patient has a history of upper respiratory surgery, airway obstruction may occur and be fatal. Patients who experience these effects, even without respiratory distress, require prolonged observation since treatment with antihistamines and corticosteroids may not be sufficient to prevent respiratory involvement. Prompt administration of subcutaneous epinephrine solution 1:1000 (0.3 to 0.5 ml) and measures to ensure a patient airway may be necessary.

Discontinue Tekturna immediately in patients who develop angioedema, and do not readminister.

5.3 Hypotension in Volume- and/or Salt-Depleted Patients

An excessive fall in blood pressure (hypotension) was rarely seen (<1%) in patients with uncomplicated hypertension treated with Tekturna HCT in controlled trials. In patients with an activated renin-angiotensin system, such as volume- and/or salt-depleted patients receiving high doses of diuretics, symptomatic hypotension may occur. Correct these conditions prior to administration of Tekturna HCT, or the treatment should start under close medical supervision.

If an excessive fall in blood pressure occurs, place the patient in the supine position and, if necessary, given an intravenous infusion of normal saline. A transient hypotensive response is not a contraindication to further treatment, which usually can be continued without difficulty once the blood pressure has stabilized.

5.4 Patients with Severe Renal Impairment

Tekturna HCT

In patients with severe renal impairment (GFR <30 mL/min), loop diuretics are preferred to thiazides, so Tekturna HCT is not recommended.

Hydrochlorothiazide

Uptitrate slowly;in patients with renal disease, thiazides may precipitate azotemia. Cumulative effects of the drug may develop in patients with impaired renal function.

5.5 Patients with Hepatic Impairment

Hydrochlorothiazide

Uptitrate slowly; minor alterations of fluid and electrolyte balance may precipitate hepatic coma.

5.6 Hypersensitivity Reactions

Hydrochlorothiazide

Hypersensitivity reactions to hydrochlorothiazide may occur in patients with or without a history of allergy or bronchial asthma, but are more likely in patients with such a history.

5.7 Systemic Lupus Erythematosus

Hydrochlorothiazide

Thiazide diuretics have been reported to cause exacerbation or activation of systemic lupus erythematosus.

5.8 Lithium Interaction

Hydrochlorothiazide

Lithium generally should not be given with thiazides [see Drug Interaction (7)].

5.9 Serum Electrolyte Abnormalities

Tekturna HCT

In the short-term controlled trials of various doses of Tekturna HCT the incidence of hypertensive patients who developed hypokalemia (serum potassium <3.5 mEq/L) was 2.2%; the incidence of hyperkalemia (serum potassium >5.5 mEq/L) was 0.8%. No patients discontinued due to increase or decrease of serum potassium.

Periodic determinations of serum electrolytes to detect possible electrolyte imbalance should be performed at appropriate intervals. The intervals should be based on the history of electrolyte abnormalities in patients with aliskiren or hydrochlorothiazide monotherapy.

Based on experience with the use of other substances that affect the renin-angiotensin system (RAS), concomitant use of Tekturna HCT with potassium-sparing diuretics, potassium supplements, salt substitutes containing potassium, or other drugs that increase potassium levels may lead to increases in serum potassium.

5.10 Renal Artery Stenosis

No data are available on the use of Tekturna HCT in patients with unilateral or bilateral renal artery stenosis or stenosis of the artery to a solitary kidney.

5.11 Cyclosporine

Aliskiren

When aliskiren was given with cyclosporine, the blood concentrations of aliskiren were significantly increased. Concomitant use of aliskiren with cyclosporine is not recommended [see Drug Interactions (7)].

6 ADVERSE REACTIONS

6.1 Clinical Studies Experience

The following serious adverse reactions are discussed in greater detail in other sections of the label:

- Risk of fetal/neonatal morbidity and mortality [see Warnings and Precautions (5.1)]
- Head and neck angioedema [see Warnings and Precautions (5.2)]
- Hypotension in volume- and/or salt-depleted patients [see Warnings and Precautions (5.3)]

Because clinical trials are conducted under widely varying conditions, adverse reaction rates observed in the clinical trials of a drug cannot be directly compared to rates in clinical trials of another drug and may not reflect the rates observed in practice.

Tekturna HCT

Tekturna HCT has been evaluated for safety in more than 2,700 patients, including over 700 treated for 6 months and 190 for over 1 year. In placebo-controlled clinical trials, discontinuation of therapy due to a clinical adverse event (including uncontrolled hypertension) occurred in 2.7% of patients treated with Tekturna HCT versus 3.6% of patients given placebo.

Adverse events in placebo-controlled trials that occurred in at least 1% of patients treated with Tekturna HCT and at a higher incidence than placebo included dizziness (2.3% vs. 1%), influenza (2.3% vs. 1.6%), diarrhea (1.6% vs. 0.5%), cough (1.3% vs. 0.5%), vertigo (1.2% vs. 0.5%), asthenia (1.2% vs. 0%), and arthralgia (1% vs. 0.5%).

Aliskiren

Aliskiren has been evaluated for safety in 6,460 patients, including 1,740 treated for longer than 6 months, and 1,250 for longer than 1 year. In placebo-controlled clinical trials, discontinuation of therapy due to a clinical adverse event, including uncontrolled hypertension occurred in 2.2% of patients treated with aliskiren, versus 3.5% of patients given placebo.

Two cases of angioedema with respiratory symptoms were reported with aliskiren use in the clinical studies. Two other cases of periorbital edema without respiratory symptoms were reported as possible angioedema and resulted in discontinuation. The rate of these angioedema cases in the completed studies was 0.06%.

In addition, 26 other cases of edema involving the face, hands, or whole body were reported with aliskiren use, including 4 leading to discontinuation.

In the placebo-controlled studies, however, the incidence of edema involving the face, hands, or whole body was 0.4% with aliskiren compared with 0.5% with placebo. In a long-term active-controlled study with aliskiren and HCTZ arms, the incidence of edema involving the face, hands, or whole body was 0.4% in both treatment arms.

Aliskiren produces dose-related gastrointestinal (GI) adverse reactions. Diarrhea was reported by 2.3% of patients at 300 mg, compared to 1.2% in placebo patients. In women and the elderly (age ≥65) increases in diarrhea rates were evident starting at a dose of 150 mg daily, with rates for these subgroups at 150 mg comparable to those seen at 300 mg for men or younger patients (all rates about 2% to 2.3%). Other GI symptoms included abdominal pain, dyspepsia, and gastroesophageal reflux, although increased rates for abdominal pain and dyspepsia were distinguished from placebo only at 600 mg daily. Diarrhea and other GI symptoms were typically mild and rarely led to discontinuation.

Aliskiren was associated with a slight increase in cough in the placebo-controlled studies (1.1% for any aliskiren use vs. 0.6% for placebo). In active-controlled trials with ACE inhibitor (ramipril, lisinopril) arms, the rates of cough for the aliskiren arms were about one-third to one-half the rates in the ACE inhibitor arms.

Other adverse reactions with increased rates for aliskiren compared to placebo included rash (1% vs. 0.3%), elevated uric acid (0.4% vs. 0.1%), gout (0.2% vs. 0.1%), and renal stones (0.2% vs. 0%).

Single episodes of tonic-clonic seizures with loss of consciousness were reported in two patients treated with aliskiren in the clinical trials. One patient had predisposing causes for seizures and had a negative electroencephalogram (EEG) and cerebral imaging following the seizures; for the other patient, EEG and imaging results were not reported. Aliskiren was discontinued and there was no rechallenge in either case.

The following adverse events occurred in placebo-controlled clinical trials at an incidence of more than 1% of patients treated with aliskiren, but also occurred at about the same or greater incidence in patients receiving placebo: headache, nasopharyngitis, dizziness, fatigue, upper respiratory tract infection, back pain and cough.

No clinically meaningful changes in vital signs or in ECG (including QTc interval) were observed in patients treated with aliskiren.

Hydrochlorothiazide

Other adverse reactions that have been reported with hydrochlorothiazide, without regard to causality, are listed below:

Body As A Whole: weakness

Digestive: pancreatitis, jaundice (intrahepatic cholestatic jaundice), sialadenitis, cramping, gastric irritation

Hematologic: aplastic anemia, agranulocytosis, leukopenia, hemolytic anemia, thrombocytopenia;

Hypersensitivity: purpura, photosensitivity, urticaria, necrotizing angiitis (vasculitis and cutaneous vasculitis), fever, respiratory distress including pneumonitis and pulmonary edema, anaphylactic reactions

Metabolic: hyperglycemia, glycosuria, hyperuricemia

Musculoskeletal: muscle spasm

Nervous System/Psychiatric: restlessness

Renal: renal failure, renal dysfunction, interstitial nephritis

Skin: erythema multiforme including Stevens-Johnson syndrome, exfoliative dermatitis including toxic epidermal necrolysis

Special Senses: transient blurred vision, xanthopsia

6.2 Clinical Laboratory Test Abnormalities

In controlled clinical trials, clinically important changes in standard laboratory parameters were rarely associated with administration of Tekturna HCT.

Blood Urea Nitrogen (BUN)/Creatinine: Elevations (greater than 50% increase) in BUN and creatinine occurred in 11.8% and 0.9%, respectively, of patients taking Tekturna HCT, and 7% and 1.1%, respectively, of patients given placebo in short-term controlled clinical trials. No patients were discontinued due to an increase in either BUN or creatinine.

Hemoglobin and Hematocrit: A greater than 20% decrease in hemoglobin and hematocrit were observed in <0.1% and 0.1%, respectively, of patients treated with Tekturna HCT, compared with 0% in placebo-treated patients. No patients were discontinued due to anemia.

Liver Function Tests: Occasional elevations (greater than 150%) in ALT (SGPT) were observed in 1.2% of patients treated with Tekturna HCT, compared with 0% in placebo-treated patients. No patients were discontinued due to abnormal liver function tests.

Serum Uric Acid: Uric acid related abnormalities were more commonly observed in patients treated with Tekturna HCT, compared with placebo; 2.2% versus 0% had a uric acid increase >50% from baseline; gout and renal stones were less commonly observed.

Serum Electrolytes: [See Warnings and Precautions (5.8).]

6.3 Post-Marketing Experience

The following adverse reactions have been reported in aliskiren post-marketing experience. Because these reactions are reported voluntarily from a population of uncertain size, it is not always possible to reliably estimate their frequency or establish a causal relationship to drug exposure.

Hypersensitivity: angioedema requiring airway management and hospitalization

Peripheral edema

7 DRUG INTERACTIONS

No drug interaction studies have been conducted with Tekturna HCT and other drugs, although studies with the individual aliskiren and hydrochlorothiazide components are described below.

Aliskiren

Effects of Other Drugs on Aliskiren

Based on in vitro studies, aliskiren is metabolized by CYP 3A4.

Irbesartan: Coadministration of irbesartan reduced aliskiren Cmax up to 50% after multiple dosing.

P-glycoprotein Effects: Pgp (MDR1/Mdr1a/1b) was found to be the major efflux system involved in absorption and disposition of aliskiren in preclinical studies. The potential for drug interactions at the Pgp site will likely depend on the degree of inhibition of this transporter. Coadministration of aliskiren with Pgp substrates or weak to moderate inhibitors such as atenolol, digoxin, and amlodipine did not result in clinically relevant interactions.

Atorvastatin: Coadministration of atorvastatin, a weak Pgp inhibitor, resulted in about a 50% increase in aliskiren Cmax and AUC after multiple dosing.

Ketoconazole: Coadministration of 200 mg twice-daily ketoconazole, a moderate Pgp inhibitor, with aliskiren resulted in an approximate 80% increase in plasma levels of aliskiren. A 400-mg once-daily dose was not studied but would be expected to increase aliskiren blood levels further.

Cyclosporine: Coadministration of 200 mg and 600 mg cyclosporine, a potent Pgp inhibitor, with 75 mg aliskiren resulted in an approximately 2.5-fold increase in Cmax and 5-fold increase in AUC of aliskiren. Concomitant use of aliskiren with cyclosporine is not recommended.

Verapamil: Coadministration of 240 mg of verapamil, a moderate Pgp inhibitor, with 300 mg aliskiren resulted in an approximately 2-fold increase in Cmax and AUC of aliskiren. However, no dosage adjustment is necessary.

Drugs with no clinically significant effects: Coadministration of lovastatin, atenolol, warfarin, furosemide, digoxin, celecoxib, hydrochlorothiazide, ramipril, valsartan, metformin and amlodipine did not result in clinically significant increases in aliskiren exposure.

Effects of Aliskiren on Other Drugs

Aliskiren does not inhibit the CYP450 isoenzymes (CYP1A2, 2C8, 2C9, 2C19, 2D6, 2E1, and CYP 3A) or induce CYP 3A4.

Furosemide: When aliskiren was coadministered with furosemide, the AUC and Cmax of furosemide were reduced by about 30% and 50%, respectively. Patients receiving furosemide could find its effect diminished after starting aliskiren.

Drugs with no clinically significant effects: Coadministration of aliskiren did not significantly affect the pharmacokinetics of lovastatin, digoxin, valsartan, amlodipine, metformin, celecoxib, atenolol, atorvastatin, ramipril or hydrochlorothiazide.

Warfarin: The effects of aliskiren on warfarin pharmacokinetics have not been evaluated.

Hydrochlorothiazide

When administered concurrently, the following drugs may interact with thiazide diuretics.

Alcohol, barbiturates, or narcotics: Potentiation of orthostatic hypotension may occur.

Antidiabetic drugs (oral agents and insulin): Dosage adjustment of the antidiabetic drug may be required.

Other antihypertensive drugs: Additive effect or potentiation.

Cholestyramine and colestipol resins: Absorption of hydrochlorothiazide is impaired in the presence of anionic exchange resins. Single doses of either cholestyramine or colestipol resins bind the hydrochlorothiazide and reduce its absorption from the gastrointestinal tract by up to 85% and 43%, respectively.

Corticosteroids, ACTH: Intensified electrolyte depletion, particularly hypokalemia.

Pressor amines (e.g., norepinephrine): Possible decreased response to pressor amines but not sufficient to preclude their use.

Skeletal muscle relaxants, nondepolarizing (e.g., tubocurarine): Possible increased responsiveness to the muscle relaxants.

Lithium: Should not generally be given with diuretics. Diuretic agents reduce the renal clearance of lithium and increase the risk of lithium toxicity. Refer to the package insert for lithium before use of such preparation with Tekturna HCT.

Nonsteroidal anti-inflammatory drugs: In some patients, the administration of a nonsteroidal anti-inflammatory agent can reduce the diuretic, natriuretic, and antihypertensive effects of loop, potassium-sparing and thiazide diuretics. Therefore, when Tekturna HCT and nonsteroidal anti-inflammatory agents are used concomitantly, the patient should be observed closely to determine if the desired effect of the diuretic is obtained.

8 USE IN SPECIFIC POPULATIONS

8.1 Pregnancy

Pregnancy Category D [See Warnings and Precautions (5.1).]

Tekturna HCT contains both aliskiren (a direct renin inhibitor) and hydrochlorothiazide (a thiazide diuretic). When administered during the second or third trimester of pregnancy, drugs that act directly on the renin-angiotensin system can cause fetal and neonatal morbidity and death.

Thiazides can cross the placenta, and use of thiazides during pregnancy is associated with a risk of fetal or neonatal jaundice, thrombocytopenia, and possibly other adverse reactions that have occurred in adults. Tekturna HCT can cause fetal harm when administered to a pregnant woman. If this drug is used during pregnancy, or if the patient becomes pregnant while taking this drug, apprise the patient of the potential hazard to the fetus.

In several dozen published cases, ACE inhibitor use during the second and third trimesters of pregnancy was associated with fetal and neonatal injury, including hypotension, neonatal skull hypoplasia, anuria, reversible or irreversible renal failure, and death. Oligohydramnios was also reported, presumably from decreased fetal renal function. In this setting, oligohydramnios was associated with fetal limb contractures, craniofacial deformation, and hypoplastic lung development. Prematurity, intrauterine growth retardation, and patent ductus arteriosus were also reported, although it is not clear whether these occurrences were due to exposure to the drug. In addition, first trimester use of ACE inhibitors, a specific class of drugs acting on the renin-angiotensin system, has been associated with a potential risk of birth defects in retrospective data.

When pregnancy occurs in a patient using Tekturna HCT, the physician should discontinue Tekturna HCT treatment as soon as possible. The physician should inform the patient about potential risks to the fetus based on the time of gestational exposure to Tekturna HCT (first trimester only or later). If exposure occurs beyond the first trimester, an ultrasound examination should be done.

In rare cases when another antihypertensive agent cannot be used to treat the pregnant patient, serial ultrasound examinations should be performed to assess the intraamniotic environment. Routine fetal testing with non-stress tests, biophysical profiles, and/or contraction stress tests may be appropriate based on gestational age and standards of care in the community. If oligohydramnios occurs in these situations, individualized decisions about continuing or discontinuing Tekturna HCT treatment and about pregnancy management should be made by the patient, her physician, and experts in the management of high risk pregnancy. Patients and physicians should be aware that oligohydramnios may not appear until after the fetus has sustained irreversible injury. Infants with histories of in utero exposure to Tekturna HCT should be closely observed for hypotension, oliguria, and hyperkalemia. If oliguria occurs, these infants may require blood pressure and renal perfusion support. Exchange transfusion or dialysis may be required to reverse hypotension and/or support decreased renal function.

No reproductive toxicity studies have been conducted with the combination of aliskiren and hydrochlorothiazide. However, these studies have been conducted for aliskiren as well as hydrochlorothiazide alone.

Reproductive toxicity studies of aliskiren hemifumarate did not reveal any evidence of teratogenicity at oral doses up to 600 mg aliskiren/kg/day (20 times the maximum recommended human dose [MRHD] of 300 mg/day on a mg/m^2 basis) in pregnant rats or up to 100 mg aliskiren/kg/day (seven times the MRHD on a mg/m^2 basis) in pregnant rabbits. Fetal birth weight was adversely affected in rabbits at 50 mg/kg/day (3.2 times the MRHD on a mg/m^2 basis). Aliskiren was present in placenta, amniotic fluid and fetuses of pregnant rabbits.

When pregnant mice and rats were given hydrochlorothiazide at doses up to 3000 and 1000 mg/kg/day, respectively (about 600 and 400 times the MRHD) during their respective periods of major organogenesis, there was no evidence of fetal harm.

8.3 Nursing Mothers

It is not known whether aliskiren is excreted in human milk, but aliskiren was secreted in the milk of lactating rats. Thiazides appear in human milk. Because of the potential for adverse effects on the nursing infant, a decision should be made whether to discontinue nursing or discontinue the drug, taking into account the importance of the drug to the mother.

8.4 Pediatric Use

Safety and effectiveness in pediatric patients have not been established.

8.5 Geriatric Use

In the short-term controlled clinical trials of Tekturna HCT, 325 (19.6%) patients treated with Tekturna HCT were ≥65 years and 53 (3.2%) were ≥75 years.

No overall differences in safety or effectiveness were observed between these subjects and younger subjects, and other reported clinical experience has not identified differences in responses between the elderly and younger patients, but greater sensitivity of some older individuals cannot be ruled out.

10 OVERDOSAGE

Aliskiren

Limited data are available related to overdosage in humans. The most likely manifestation of overdosage would be hypotension. If symptomatic hypotension should occur, supportive treatment should be initiated.

Hydrochlorothiazide

The most common signs and symptoms of overdose observed in humans are those caused by electrolyte depletion (hypokalemia, hypochloremia, hyponatremia) and dehydration resulting from excessive diuresis. If digitalis has also been administered, hypokalemia may accentuate cardiac arrhythmias. The degree to which hydrochlorothiazide is removed by hemodialysis has not been established. The oral LD50 of hydrochlorothiazide is greater than 10 g/kg in both mice and rats.

11 DESCRIPTION

Tekturna HCT is a fixed combination of aliskiren, an orally active, nonpeptide, direct renin inhibitor, and hydrochlorothiazide, a thiazide diuretic.

Aliskiren

Aliskiren hemifumarate is chemically described as (2S,4S,5S,7S)-N-(2-Carbamoyl-2-methylpropyl)-5-amino-4-hydroxy-2,7-diisopropyl-8-[4-methoxy-3-(3-methoxypropoxy)phenyl]-octanamide hemifumarate and its structural formula is

Molecular formula: C30H53N3O6 • 0.5 C4H4O4

Aliskiren hemifumarate is a white to slightly yellowish crystalline powder with a molecular weight of 609.8 (free base- 551.8). It is soluble in phosphate buffer, n-Octanol, and highly soluble in water.

Hydrochlorothiazide

Hydrochlorothiazide USP is a white, or practically white, practically odorless, crystalline powder. It is slightly soluble in water; freely soluble in sodium hydroxide solution, in n-butylamine, and in dimethylformamide; sparingly soluble in methanol; and insoluble in ether, in chloroform, and in dilute mineral acids. Hydrochlorothiazide is chemically described as 6-chloro-3,4-dihydro-2H-1,2,4-benzothiadiazine-7-sulfonamide 1,1-dioxide.

Hydrochlorothiazide is a thiazide diuretic. Its empirical formula is C7H8ClN3O4S2, its molecular weight is 297.73, and its structural formula is

Tekturna HCT tablets are formulated for oral administration to contain aliskiren and hydrochlorothiazide, USP 150/12.5 mg, 150/25 mg, 300/12.5 mg and 300/25 mg. The inactive ingredients for all strengths of the tablets are colloidal silicon dioxide, crospovidone, hydroxypropyl methylcellulose, iron oxide colorants, lactose, magnesium stearate, microcrystalline cellulose, polyethylene glycol, povidone, talc, titanium dioxide, and wheat starch.

12 CLINICAL PHARMACOLOGY

12.1 Mechanism of Action

Aliskiren

Renin is secreted by the kidney in response to decreases in blood volume and renal perfusion. Renin cleaves angiotensinogen to form the inactive decapeptide angiotensin I (Ang I). Ang I is converted to the active octapeptide angiotensin II (Ang II) by angiotensin-converting enzyme (ACE) and non-ACE pathways. Ang II is a powerful vasoconstrictor and leads to the release of catecholamines from the adrenal medulla and prejunctional nerve endings. It also promotes aldosterone secretion and sodium reabsorption. Together, these effects increase blood pressure. Ang II also inhibits renin release, thus providing a negative feedback to the system. This cycle, from renin through angiotensin to aldosterone and its associated negative feedback loop, is known as the renin-angiotensin-aldosterone system (RAAS). Aliskiren is a direct renin inhibitor, decreasing plasma renin activity (PRA) and inhibiting the conversion of angiotensinogen to Ang I. Whether aliskiren affects other RAAS components, e.g., ACE or non-ACE pathways, is not known.

All agents that inhibit the RAAS, including renin inhibitors, suppress the negative feedback loop, leading to a compensatory rise in plasma renin concentration. When this rise occurs during treatment with ACE inhibitors and ARBs, the result is increased levels of PRA. During treatment with aliskiren, however, the effect of increased renin levels is blocked, so that PRA, Ang I and Ang II are all reduced, whether aliskiren is used as monotherapy or in combination with other antihypertensive agents.

Hydrochlorothiazide

Hydrochlorothiazide is a thiazide diuretic. Thiazides affect the renal tubular mechanisms of electrolyte reabsorption, directly increasing excretion of sodium and chloride in approximately equivalent amounts. Indirectly, the diuretic action of hydrochlorothiazide reduces plasma volume, with consequent increases in plasma renin activity, increases in aldosterone secretion, increases in urinary potassium loss, and decreases in serum potassium. The renin-aldosterone link is mediated by angiotensin II, so coadministration of agents that block the production or function of angiotensin II tends to reverse the potassium loss associated with these diuretics.

The mechanism of action of the antihypertensive effect of thiazides is unknown.

12.2 Pharmacodynamics

Tekturna HCT

In placebo-controlled clinical trials, PRA was decreased with aliskiren monotherapy (ranging from 54% to 65%) and increased with hydrochlorothiazide monotherapy (ranging from 4% to 72%). Treatment with Tekturna HCT resulted in PRA reductions ranging from approximately 46% to 63% in various doses despite the increase in PRA with hydrochlorothiazide treatment. The clinical implications of the differences in effect on PRA are not known.

Aliskiren

PRA reductions in clinical trials ranged from approximately 50% to 80%, were not dose-related and did not correlate with blood pressure reductions. The clinical implications of the differences in effect on PRA are not known.

Hydrochlorothiazide

After oral administration of hydrochlorothiazide, diuresis begins within 2 hours, peaks in about 4 hours, and lasts about 6 to 12 hours.

12.3 Pharmacokinetics

Absorption and Distribution

Tekturna HCT

Following oral administration of Tekturna HCT combination tablets, the median peak plasma concentration time are within 1 hour for aliskiren and 2.5 hours for hydrochlorothiazide. When taken with food, mean AUC and Cmax of aliskiren are decreased by 60% and 82%, respectively; mean AUC and Cmax of hydrochlorothiazide increased by 13% and 10%, respectively. As a result, patients should establish a routine pattern for taking Tekturna HCT with regard to meals and should be advised that high-fat meals decrease absorption of aliskiren substantially.

Hydrochlorothiazide

Hydrochlorothiazide crosses the placental but not the blood-brain barrier and is excreted in breast milk.

Metabolism and Elimination

Aliskiren

About one-fourth of the absorbed dose appears in the urine as parent drug. How much of the absorbed dose is metabolized is unknown. Based on the in vitro studies, the major enzyme responsible for aliskiren metabolism appears to be CYP 3A4.

Hydrochlorothiazide

Hydrochlorothiazide is not metabolized but is eliminated rapidly by the kidney. At least 61% of the oral dose is eliminated as unchanged drug within 24 hours. The elimination half-life is between 5.8 and 18.9 hours.

Special Populations

Pediatric Patients

The pharmacokinetics of aliskiren have not been investigated in patients <18 years of age.

Geriatric Patients

The pharmacokinetics of aliskiren were studied in the elderly (≥65 years). Exposure (measured by AUC) is increased in elderly patients. Adjustment of the starting dose is not required in these patients [see Dosage and Administration (2)].

Race

Too few non-Caucasians have been studied with Tekturna HCT to assess pharmacokinetic differences among races. The pharmacokinetic differences among Blacks, Caucasians, and Japanese are minimal with aliskiren therapy.

Renal Impairment

The pharmacokinetics of aliskiren were evaluated in patients with varying degrees of renal impairment. Rate and extent of exposure (AUC and Cmax) of aliskiren in subjects with renal impairment did not show a consistent correlation with the severity of renal impairment. Adjustment of the starting dose is not required in patients with mild or moderate renal impairment, but Tekturna HCT is not recommended in patients with severe renal impairment [see Dosage and Administration (2) and Warnings and Precautions (5.4)].

Hepatic Impairment

The pharmacokinetics of aliskiren were not significantly affected in patients with mild-to-severe liver disease. Consequently, adjustment of the starting dose is not required in these patients [see Dosage and Administration (2)].

13 NONCLINICAL TOXICOLOGY

13.1 Carcinogenesis, Mutagenesis, Impairment of Fertility

Tekturna HCT

No carcinogenicity, mutagenicity or fertility studies have been conducted with Tekturna HCT. However, these studies have been conducted for aliskiren as well as hydrochlorothiazide alone.

Aliskiren

Carcinogenic potential was assessed in a 2-year rat study and a 6-month transgenic (rasH2) mouse study with aliskiren hemifumarate at oral doses of up to 1500 mg aliskiren/kg/day. Although there were no statistically significant increases in tumor incidence associated with exposure to aliskiren, mucosal epithelial hyperplasia (with or without erosion/ulceration) was observed in the lower gastrointestinal tract at doses of 750 or more mg/kg/day in both species, with a colonic adenoma identified in one rat and a cecal adenocarcinoma identified in another, rare tumors in the strain of rat studied. On a systemic exposure (AUC0-24hr) basis, 1500 mg/kg/day in the rat is about 4 times and in the mouse about 1.5 times the maximum recommended human dose (300 mg aliskiren/day). Mucosal hyperplasia in the cecum or colon of rats was also observed at doses of 250 mg/kg/day (the lowest tested dose) as well as at higher doses in 4- and 13-week studies.

Aliskiren hemifumarate was devoid of genotoxic potential in the Ames reverse mutation assay with S. typhimurium and E. coli, the in vitro Chinese hamster ovary cell chromosomal aberration assay, the in vitro Chinese hamster V79 cell gene mutation test and the in vivo mouse bone marrow micronucleus assay.

Fertility of male and female rats was unaffected at doses of up to 250 mg aliskiren/kg/day (8 times the maximum recommended human dose of 300 mg Tekturna/60 kg on a mg/m^2 basis.

Hydrochlorothiazide

Two-year feeding studies in mice and rats conducted under the auspices of the National Toxicology Program (NTP) uncovered no evidence of a carcinogenic potential of hydrochlorothiazide in female mice (at doses of up to approximately 600 mg/kg/day) or in male and female rats (at doses of up to approximately 100 mg/kg/day). The NTP, however, found equivocal evidence for hepatocarcinogenicity in male mice.

Hydrochlorothiazide was not genotoxic in vitro in the Ames mutagenicity assay of S. typhimurium strains TA 98, TA 100, TA 1535, TA 1537, and TA 1538 and in the Chinese Hamster Ovary (CHO) test for chromosomal aberrations, or in vivo in assays using mouse germinal cell chromosomes, Chinese hamster bone marrow chromosomes, and the Drosophila sex-linked recessive lethal trait gene. Positive test results were obtained only in the in vitro CHO Sister Chromatid Exchange (clastogenicity) and in the Mouse Lymphoma Cell (mutagenicity) assays, using concentrations of hydrochlorothiazide from 43 to 1300 mcgm/mL, and in the Aspergillums Nidulans nondisjunction assay at an unspecified concentration.

Hydrochlorothiazide had no adverse effects on the fertility of mice and rats of either sex in studies wherein these species were exposed, via their diet, to doses of up to 100 and 4 mg/kg, respectively, prior to mating and throughout gestation. These doses of hydrochlorothiazide in mice and rats represent 19 and 1.5 times, respectively, the maximum recommended human dose on a mg/m^2 basis. (Calculations assume an oral dose of 25 mg/day and a 60-kg patient.)

14 CLINICAL STUDIES

Tekturna HCT

In all clinical trials including over 6,200 patients, more than 2,700 patients were exposed to combinations of aliskiren and hydrochlorothiazide. The safety and efficacy of Tekturna HCT were evaluated in patients with mild-to-moderate hypertension in an 8-week, randomized, double-blind, placebo-controlled, parallel-group, 15-arm factorial trial (n=2762). Patients were randomized to receive various combinations of aliskiren (75 mg to 300 mg) plus hydrochlorothiazide (6.25 mg to 25 mg) once daily (without titrating up from monotherapy) and followed for blood pressure response. The combination of aliskiren and hydrochlorothiazide resulted in additive placebo-adjusted decreases in systolic and diastolic blood pressure at trough of 10-14/5-7 mmHg at doses of 150-300 mg/12.5-25 mg, compared to 5-8/2-3 mmHg for aliskiren 150 mg to 300 mg and 6-7/2-3 mmHg for hydrochlorothiazide 12.5 mg to 25 mg, alone. Blood pressure reductions with the combinations were greater than the reductions with the monotherapies as shown in Table 1.

Table 1: Placebo-Subtracted Reductions in Seated Trough Cuff Blood Pressure in Combination with Hydrochlorothiazide
 |  | Hydrochlorothiazide, mg
 |  | 0 | 6.25 | 12.5 | 25
Aliskiren, mg | Placebo Mean Change | Placebo-subtracted | Placebo-subtracted | Placebo-subtracted | Placebo-subtracted
0 | 7.5/6.9 | -- | 3.5/2.1 | 6.4/3.2 | 6.8/2.4
75 | -- | 1.9/1.8 | 6.8/3.8 | 8.2/4.2 | 9.8/4.5
150 | -- | 4.8/2 | 7.8/3.4 | 10.1/5 | 12/5.7
300 | -- | 8.3/3.3 | -- | 12.3/7 | 13.7/7.3

The safety and efficacy of Tekturna HCT as initial therapy was evaluated in this trial. All patients randomized to the combination groups received the combination treatment of Tekturna HCT at assigned doses as initial therapy without titration from monotherapy. The figures [see Indications and Usage (1)] display the probability that a patient will achieve systolic or diastolic blood pressure goal with Tekturna HCT 300/25 mg, based upon their baseline systolic or diastolic blood pressure. At all levels of baseline blood pressure, the probability of achieving any given diastolic or systolic goal is greater with the combination than for either monotherapy..

The antihypertensive effect of Tekturna HCT was largely manifested within 1 week. The maximum antihypertensive effect was generally attained after about 4 weeks of therapy.

One active-controlled trial investigated the addition of 300 mg aliskiren in obese hypertensive patients who did not respond adequately to hydrochlorothiazide 25 mg, and showed incremental decreases of systolic and diastolic blood pressure of approximately 7/4 mmHg.

In long-term follow-up studies (without placebo control) the effect of the combination of aliskiren and hydrochlorothiazide was maintained for over 1 year.

The antihypertensive effect was independent of age and gender. There were too few non-Caucasians to assess differences in blood pressure effects by race.

Aliskiren Monotherapy

The antihypertensive effects of aliskiren have been demonstrated in six randomized, double-blind, placebo-controlled, 8-week clinical trials in patients with mild-to-moderate hypertension. The placebo response and placebo-subtracted changes from baseline in seated trough cuff blood pressure are shown in Table 2.

Table 2: Reductions in Seated Trough Cuff Blood Pressure in the Placebo-Controlled Studies of Aliskiren Monotherapy
 |  | Aliskiren Daily Dose, mg
 |  | 75 | 150 | 300 | 600
Study | Placebo Mean Change | Placebo-subtracted | Placebo-subtracted | Placebo-subtracted | Placebo-subtracted
1 | 2.9/3.3 | 5.7/4* | 5.9/4.5* | 11.2/7.5* | --
2 | 5.3/6.3 | -- | 6.1/2.9* | 10.5/5.4* | 10.4/5.2*
3 | 10/8.6 | 2.2/1.7 | 2.1/1.7 | 5.1/3.7* | --
4 | 7.5/6.9 | 1.9/1.8 | 4.8/2* | 8.3/3.3* | --
5 | 3.8/4.9 | -- | 9.3/5.4* | 10.9/6.2* | 12.1/7.6*
6 | 4.6/4.1 | -- | -- | 8.4/4.9† | --
*p<0.05 vs. placebo by ANCOVA with Dunnett’s procedure for multiple comparisons.
†p<0.05 vs. placebo by ANCOVA for the pairwise comparison.

The studies included approximately 2,730 patients given doses of 75 mg to 600 mg of aliskiren and 1,231 patients given placebo. As shown in Table 2, there is some increase in response with administered dose in all studies, with reasonable effects seen at 150 mg to 300 mg, and no clear further increase at 600 mg. A substantial proportion (85% to 90%) of the blood pressure lowering effect was observed within 2 weeks of treatment. Studies with ambulatory blood pressure monitoring showed reasonable control throughout the interdosing interval, e.g., the ratios of mean daytime to mean nighttime ambulatory BP ranged from 0.6 to 0.9.

Patients in the placebo-controlled trials continued open-label aliskiren for up to one year. A persistent blood pressure lowering effect was demonstrated by a randomized withdrawal study (patients randomized to continued drug or placebo), which showed a statistically significant difference between patients kept on aliskiren and those randomized to placebo. With cessation of treatment, blood pressure gradually returned toward baseline levels over a period of several weeks. There was no evidence of rebound hypertension after abrupt cessation of therapy.

The effectiveness of aliskiren was demonstrated across all demographic subgroups, although Black patients tended to have smaller reductions in blood pressure than Caucasians and Asians, as has been seen with ACE inhibitors and ARBs.

Aliskiren in Combination with Other Antihypertensives

Valsartan

Aliskiren 150 mg and 300 mg and valsartan 160 mg and 320 mg were studied alone and in combination in an 8-week, 1,797-patient, randomized, double-blind, placebo-controlled, parallel-group, 4-arm, dose-escalation study. The dosages of aliskiren and valsartan were started at 150 mg and 160 mg, respectively, and increased at four weeks to 300 mg and 320 mg, respectively. Seated trough cuff blood pressure was measured at baseline, 4, and 8 weeks. Blood pressure reductions with the combinations were greater than the reductions with the monotherapies as shown in Table 3.

Table 3: Placebo-Subtracted Reductions in Seated Trough Cuff Blood Pressure of Aliskiren in Combination with Valsartan
 |  | Valsartan, mg
Aliskiren, mg | Placebo Mean Change | 0 | 160 | 320
0 | 4.6/4.1* | -- | 5.6/3.9 | 8.2/5.6
150 | -- | 5.4/2.7 | 10.0/5.7 | --
300 | -- | 8.4/4.9 | -- | 12.6/8.1
* The placebo change is 5.2/4.8 for Week 4 endpoint which was used for the dose groups containing aliskiren 150 mg or valsartan 160 mg.

ACE Inhibitors and Amlodipine

Aliskiren has not been studied when added to maximal doses of ACE inhibitors to determine whether aliskiren produces additional blood pressure reduction with a maximal dose of an ACE inhibitor. Aliskiren 150 mg provided additional blood pressure reduction when coadministered with amlodipine 5 mg in one study, but the combination was not statistically significantly better than amlodipine 10 mg.

16 HOW SUPPLIED/STORAGE AND HANDLING

Tekturna HCT is supplied as biconvex, ovaloid film-coated tablets.

All strengths are packaged in bottles as described below.

Table 4: Tekturna HCT Tablets Supply
Tablet | Color | Imprint | Imprint | NDC #
Aliskiren/HCTZ |  | Side 1 | Side 2 | Bottle of 30 | Bottle of 90
150 mg/12.5 mg | White | NVR | LCI | 54868-6041-0 | --
300 mg/12.5 mg | Violet White | NVR | CVI | -- | 54868-6103-0
300 mg/25 mg | Light Yellow | NVR | CVV | -- | 54868-6194-0

Storage

Store at 25ºC (77ºF); excursions permitted to 15-30ºC (59-86ºF) [see USP Controlled Room Temperature].

Protect from moisture.

Dispense in tight container (USP).

17 PATIENT COUNSELING INFORMATION

Healthcare professionals should instruct their patients to read the Patient Package Insert before starting Tekturna HCT and to reread each time the prescription is renewed. Patients should be instructed to inform their doctor or pharmacist if they develop any unusual symptom, or if any known symptom persists or worsens.

Pregnancy

Female patients of childbearing age should be told about the consequences of exposure to drugs that act on the renin-angiotensin system. Discuss other treatment options with female patients planning to become pregnant. These patients should be asked to report pregnancies to their physicians as soon as possible.

Symptomatic Hypotension

A patient receiving Tekturna HCT should be cautioned that lightheadedness can occur, especially during the first days of therapy, and that it should be reported to the prescribing physician. The patients should be told that if syncope occurs, Tekturna HCT should be discontinued until the physician has been consulted.

All patients should be cautioned that inadequate fluid intake, excessive perspiration, diarrhea, or vomiting can lead to an excessive fall in blood pressure, with the same consequences of lightheadedness and possible syncope.

Potassium Supplements

A patient receiving Tekturna HCT should be told not to use potassium supplements or salt substitutes containing potassium without consulting the prescribing physician.

Relationship to Meals

Patients should establish a routine pattern for taking Tekturna HCT with regard to meals. High-fat meals decrease absorption substantially.

Patient Information

Tekturna HCT® (tek-turn-a HCT)

(aliskiren and hydrochlorothiazide, USP)

Combination Tablets

Read the Patient Information that comes with Tekturna HCT before you start taking it and each time you get a refill. There may be new information. This leaflet does not take the place of talking with your doctor about your condition and treatment.

IMPORTANT WARNING: Tekturna HCT may harm an unborn baby, causing injury and even death. If you get pregnant, stop taking Tekturna HCT and call your doctor right away. If you plan to become pregnant, talk to your doctor about other medicines to treat your high blood pressure before taking Tekturna HCT.

What is Tekturna HCT?

Tekturna HCT contains two prescription medicines in one tablet that work together to lower blood pressure. It contains:

- aliskiren (Tekturna), a direct renin inhibitor (DRI)
- hydrochlorothiazide, a diuretic (water pill)

Aliskiren (Tekturna) reduces the effect of renin, and the harmful process that narrows blood vessels. Aliskiren also helps blood vessels relax and widen so blood pressure is lower. Hydrochlorothiazide reduces the amount of salt and water in your body so your blood pressure is lower.

Tekturna HCT may be used to lower high blood pressure in adults

- when one medicine to lower high blood pressure is not enough
- as the first medicine to lower high blood pressure if your doctor decides that you are likely to need more than one medicine

Tekturna HCT has not been studied in children under 18 years of age.

Your doctor may prescribe other medicines for you to take along with Tekturna HCT to treat your high blood pressure.

What is high blood pressure (hypertension)?

Blood pressure is the force that pushes the blood through your blood vessels to all the organs of your body. You have high blood pressure when the force of your blood moving through your blood vessels is too great. One cause of high blood pressure is renin, a chemical in the body that starts a process that makes blood vessels narrow, leading to high blood pressure.

Tekturna HCT reduces high blood pressure. Medicines that lower your blood pressure lower your chance of having a stroke or heart attack. High blood pressure makes the heart work harder to pump blood throughout the body and causes damage to the blood vessels. If high blood pressure is not treated, it can lead to stroke, heart attack, heart failure, kidney failure, and vision problems.

Who should not take Tekturna HCT?

- If you get pregnant, stop taking Tekturna HCT and call your doctor right away. If you plan to become pregnant, talk to your doctor about other treatment options for your high blood pressure.
- Do not take Tekturna HCT if you make very little or no urine due to kidney problems.
- Do not take Tekturna HCT if you are allergic to any of its ingredients. See the end of this leaflet for a complete list of the ingredients in Tekturna HCT.

What should I tell my doctor before taking Tekturna HCT?

Tell your doctor about all your medical conditions, including whether you:

- are pregnant or planning to become pregnant. See IMPORTANT WARNING.
- have any allergies or asthma
- have kidney problems
- have liver problems
- have systemic lupus erythematosus (SLE). Tekturna HCT can make your SLE active or worse.
- have ever had a reaction called angioedema, to an ACE inhibitor medicine. Angioedema causes swelling of the face, lips, tongue, throat, arms and legs, and may cause difficulty breathing.
- are breast-feeding. It is not known if Tekturna HCT passes into your breast milk.
- Take Tekturna HCT exactly as prescribed by your doctor. It is important to take Tekturna HCT every day to control your blood pressure.

Tell your doctor about all the medicines you take including prescription and nonprescription medicines, vitamins and herbal supplements. Especially tell your doctor if you are taking:

- other medicines for high blood pressure or a heart problem
- atorvastatin (medicine to lower cholesterol in your blood)
- water pills (also called “diuretics”)
- medicines for treating fungus or fungal infections
- cyclosporine (a medicine used to suppress the immune system)
- potassium-containing medicines, potassium supplements, or salt substitutes containing potassium
- cholestyramine (for example; Questran, Questran Light, Cholestyramine Light, Locholest Light, Locholest, Prevalite) (medicines to lower the cholesterol in your blood)
- colestipol (for example; Colestipol hydrochloride, Colestid, Flavored Colestid) (medicines to lower the cholesterol in your blood)
- potassium supplements
- medicines to treat diabetes, including insulin
- lithium, a medicine used in some types of depression. Do not take Tekturna HCT if you are taking lithium.
- Nonsteroidal anti-inflammatory (NSAIDs) medicines. Ask your doctor if you are not sure if you are taking one of these medicines.
- blood thinners
- barbiturate or narcotic medicines. Ask your doctor if you are not sure if you are taking one of these medicines.

Your doctor or pharmacist will know what medicines are safe to take together. Know your medicines. Keep a list of your medicines and show it to your doctor or pharmacist when you get a new medicine.

How should I take Tekturna HCT?

- Take Tekturna HCT once each day, about the same time each day.
- Take Tekturna HCT the same way everyday, either with or without a meal.
- Your doctor may change your dose of Tekturna HCT if needed.
- If you miss a dose of Tekturna HCT, take it as soon as you remember. If it is close to your next dose, do not take the missed dose. Just take the next dose at your regular time.
- If you take too much Tekturna HCT, call your doctor or a Poison Control Center, or go to the nearest hospital emergency room.

What are the possible side effects of Tekturna HCT?

Tekturna HCT may cause serious side effects:

- Injury or death to an unborn baby. See IMPORTANT WARNING.
- Low blood pressure (hypotension). Your blood pressure may get too low if you also take water pills, are on a low-salt diet, get dialysis treatments, have heart problems, or get sick with vomiting or diarrhea. Drinking alcohol and taking certain medicines (barbiturates or narcotics) can cause low blood pressure to get worse. Lie down if you feel faint or dizzy, and call your doctor right away.
- Angioedema. Aliskiren in Tekturna HCT can cause swelling of the face, lips, tongue, throat, arms and legs, or the whole body. Get medical help right away and tell your doctor if you get any one or more of these symptoms. Angioedema can happen at any time while you are taking Tekturna HCT.
- Active or worsened Systemic Lupus Erythematosus (SLE). If you have SLE, tell your doctor right away if you get any new or worse symptoms.

Common side effects of Tekturna HCT include:

- dizziness
- flu-like symptoms
- diarrhea
- cough
- tiredness

Other less common side effects include skin rash.

Tell your doctor if you have any side effect that bothers you or that does not go away. These are not all of the possible side effects of Tekturna HCT. For a complete list of side effects, ask your doctor or pharmacist.

How do I store Tekturna HCT?

- Store Tekturna HCT tablets at room temperature between 59oF-86oF (15oC-30oC).
- Keep Tekturna HCT in the original prescription bottle in a dry place. Do not remove the desiccant (drying agent) from the bottle.

Keep Tekturna HCT and all medicines out of the reach of children.

General information about Tekturna HCT

Medicines are sometimes prescribed for conditions not listed in the patient information leaflet. Do not take Tekturna HCT for a condition for which it was not prescribed. Do not give Tekturna HCT to other people, even if they have the same condition or symptoms you have. It may harm them.

This leaflet summarizes the most important information about Tekturna HCT. If you have questions about Tekturna HCT talk with your doctor. You can ask your doctor or pharmacist for information that is written for healthcare professionals.

For more information about Tekturna HCT, visit www.TekturnaHCT.com, or call 1-888-669-6682.

What are the ingredients in Tekturna HCT?

Active ingredients: Aliskiren and hydrochlorothiazide

Inactive ingredients: Colloidal silicon dioxide, crospovidone, hydroxypropyl methylcellulose, iron oxide colorants, lactose, magnesium stearate, microcrystalline cellulose, polyethylene glycol, povidone, talc, and titanium dioxide, and wheat starch

Call your doctor for medical advice about side effects. You may report side effects to FDA at 1-800-FDA-1088.

Distributed by:

Novartis Pharmaceuticals Corporation

East Hanover, New Jersey 07936

REV: February 2010 T2010-16/T2010-17

© Novartis

Relabeling of "Additional Barcode" by:
Physicians Total Care, Inc.
Tulsa, OK 74146

PRINCIPAL DISPLAY PANEL

Package Label – 150 mg / 12.5 mg

Rx Only

Tektruna HCT®

(aliskiren and hydrochlorothiazide)

Package Label – 300 mg / 12.5 mg

Rx Only

Tektruna HCT®

(aliskiren and hydrochlorothiazide)

Package Label – 300 mg / 25 mg

Rx Only

Tektruna HCT®

(aliskiren and hydrochlorothiazide)